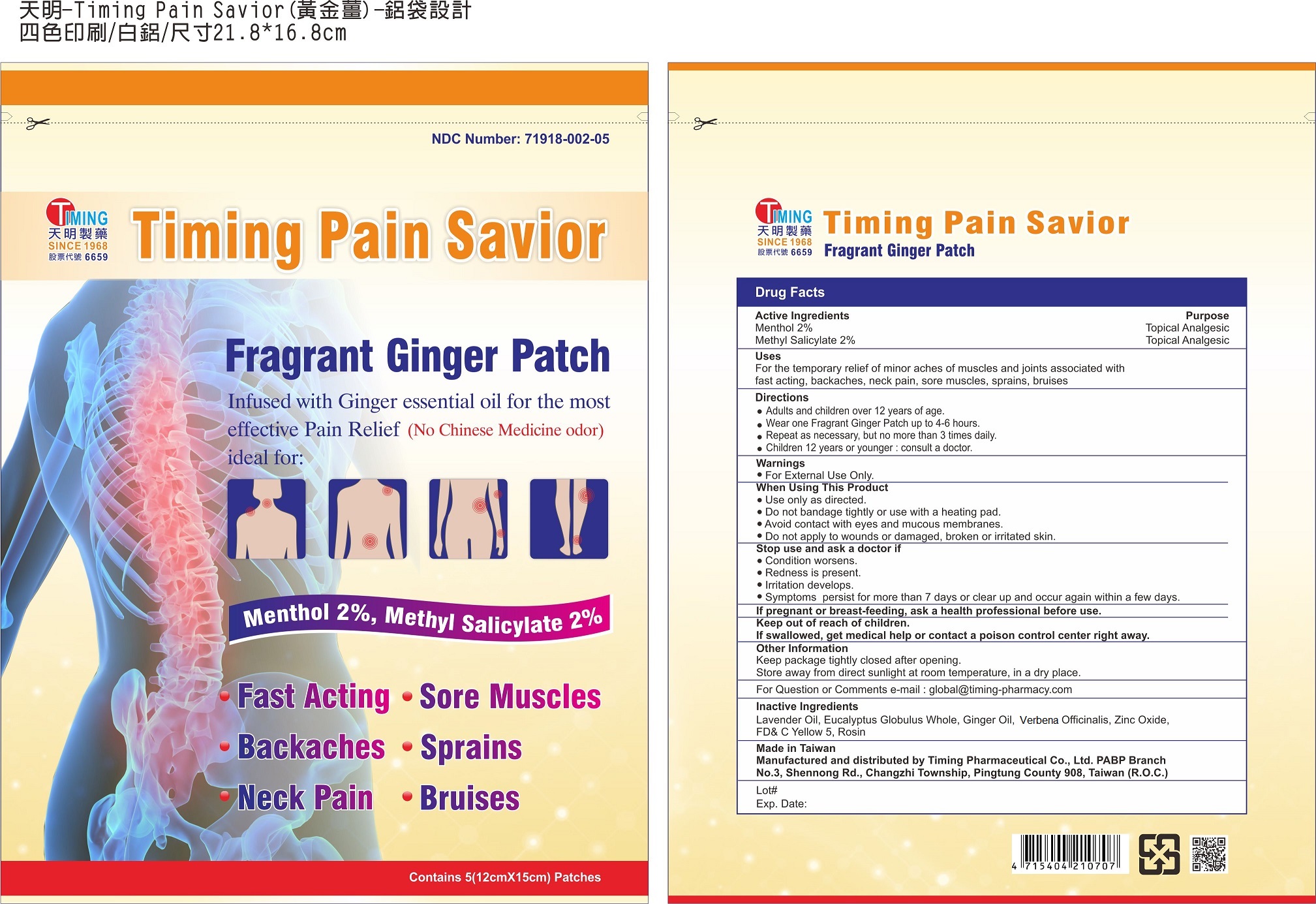 DRUG LABEL: Timing Pain Savior Fragrant Ginger Patch
NDC: 71918-002 | Form: PATCH
Manufacturer: Timing Pharmaceutical Co., Ltd PABP Branch
Category: otc | Type: HUMAN OTC DRUG LABEL
Date: 20260114

ACTIVE INGREDIENTS: MENTHOL 2 g/100 g; METHYL SALICYLATE 2 g/100 g
INACTIVE INGREDIENTS: LAVENDER OIL; EUCALYPTUS GLOBULUS WHOLE; GINGER OIL; VERBENA OFFICINALIS; ZINC OXIDE; FD&C YELLOW NO. 5; ROSIN

Timing Pharmaceutical Co., Ltd PABP Branch

Active Ingredients

Menthol 2%

Methyl Salicylate 2%

Purpose

Menthol Topical Analgesic

Methyl Salicylate Topical Analgesic

Uses

For the temporary relief of minor aches and pains of muscles and joints associated with arthritis, simple backache, strains, sprains, bruises

Directions

Adults and children over 12 years of age.
Wear one Fragrant Ginger Patch up to 4-6 hours.
Repeat as necessary, but not more than 3 times daily.
Children 12 years or younger, consult a doctor.

Warnings

For External Use Only.

When Using This Product

Use only as directed.
Do not bandage tightly or use with a heating pad.
Avoid contact with eyes and mucous membranes.
Do not apply to wounds or damaged, broken or irritated skin.

Stop Use and Ask a Doctor If

condition worsens.
redness is present.
irritation develops.
symptoms persist for more than 7 days or clear up and occur again within a few days.

Keep Out of Reach of Children.

If swallowed, get medical help or contact a Poison Control Center right away.

Other Information

Keep package tightly closed after opening.
Store away from direct sunlight at room temperature, in a dry place.

Questions or Comments?

E-mail: global@timing-pharmacy.com

Inactive Ingredients

Lavender Oil, Eucalyptus Globulus Whole, Ginger Oil, Verbena Officinalis, Zinc Oxide, FD&C Yellow #5, Rosin

Made in Taiwan

Manufactured and distributed by Timing Pharmaceutical Co., Ltd PABP Branch.
No. 3 , Shennon Rd, Changzhi Township, Pingtung County 908, Taiwan (R.O.C)